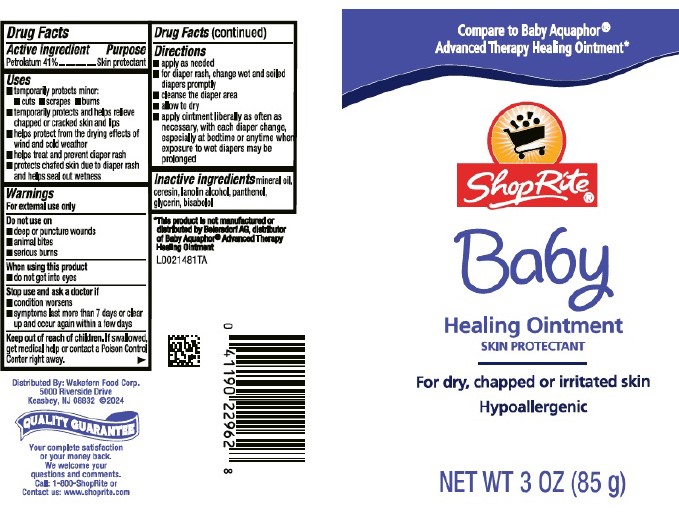 DRUG LABEL: Skin Protectant
NDC: 41190-180 | Form: OINTMENT
Manufacturer: Wakefern Food Corp.
Category: otc | Type: HUMAN OTC DRUG LABEL
Date: 20260213

ACTIVE INGREDIENTS: PETROLATUM 410 mg/1 g
INACTIVE INGREDIENTS: MINERAL OIL; CERESIN; LANOLIN ALCOHOLS; PANTHENOL; GLYCERIN; LEVOMENOL

Shop Rite 180.000/180AA-AC
Healing Ointment for Babies

Active ingredient

Petrolatum 41%

Purpose

Skin protectant

Uses

- temporarily protects minor: cuts, scrapes, burns
- temporarily protects and helps relieve chapped or cracked skin and lips
- helps protect from the drying effects of wind and cold weather
- helps treat and prevent diaper rash
- protects chafed skin due to diaper rash and helps seal out wetness

Warnings

For external use only

Do not use on

- deep or puncture wounds
- animal bites
- serious burns

When using this product

- do not get into eyes

Stop use and ask a doctor if

- condition worsens
- symptoms last more than 7 days or clear up and occur again within a few days

Keep out of reach of children.

If swallowed, get medical help or contact a Poison Control Center right away.

Directions

- apply as needed
- for diaper rash, change wet and soiled diapers promptly
- cleanse the diaper area
- allow to dry
- apply ointment liberally as often as necessary, with each diaper change, especially at bedtime or anytime when exposure to wet diapers may be prolonged

Inactive ingredients

mineral oil, ceresin, lanolin alcohol, panthenol, glycerin, bisabolol

Disclaimer

*This product is not manufactured or distributed by Beiersdorf AG, distributor of Baby Aquaphor® Advanced Therapy Healing Ointment

Adverse Reaction

Distributed By: Wakefern Food Corp.

5000 Riverside Drive

Keasbey, NJ 08832 ©2024

QUALITY GUARANTEE

Your complete satisfaction or your money back.

We welcome your questions and comments.

Call: 1-800-ShopRite or

Contact us: www.shoprite.com

Principal display panel

Compare to Baby Aquaphor® Advanced Therapy Healing Ointment*

Shop Rite®

Baby

Healing Ointment

SKIN PROTECTANT

For dry, chapped or irritated skin

Hypoallergenic

NET WT 3 OZ (85 g)